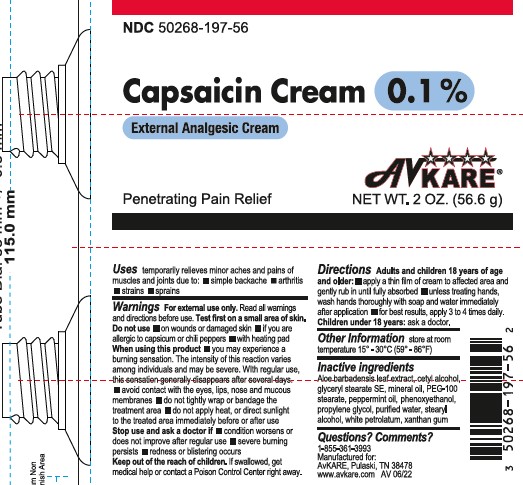 DRUG LABEL: Capsaicin
NDC: 50268-197 | Form: CREAM
Manufacturer: AvPAK
Category: otc | Type: HUMAN OTC DRUG LABEL
Date: 20260108

ACTIVE INGREDIENTS: CAPSAICIN 0.001 g/1 g
INACTIVE INGREDIENTS: WATER; CETYL ALCOHOL; PETROLATUM; PEPPERMINT OIL; PEG-100 STEARATE; PHENOXYETHANOL; GLYCERYL STEARATE SE; XANTHAN GUM; MINERAL OIL; ALOE VERA LEAF; STEARYL ALCOHOL; PROPYLENE GLYCOL

Capsaicin Cream 0.1%

Active Ingredient: Capsaicin 0.1%

Purpose: Topical Analgesic

INDICATIONS AND USAGE

Uses: Provides penetrating pain relief. Temporary relief of minor aches and pains of muscles and joints associated with simple backache, arthritis, strains, bruises, and sprains.

Warnings: For external use only.

Do not use:

- on wounds or damaged skin
- if you are allergic to capsicum or chili peppers
- with heating pad

When using this produce:

- you may experience a burning sensation The intensity of this reaction varies among individuals and may be severe. With regular use, the sensation generally disappears after several days.
- avoid contact with the eyes, lips, nose and mucous membranes
- do not tightly wrap or bandage the treatement area
- do not apply heat, or direct sunlight to the treated area immediately before or after use

Stop use and ask a doctor if:

- condition worsens or does not improve after regular use
- severe burning persists
- redness or blistering occurs

Keep out of reach of children. If product is swallowed, get medical help or contact a Poison Control Center right away.

DOSAGE AND ADMINISTRATION

Directions – Adults and children 18 years of age and older

- apply a thin film of cream to affected area and gently rub in until fully absorbed
- unless treating hands, wash hands thoroughly with soap and water immediately after application
- for best results, apply 3 to 4 times daily

Children under 18 years: ask a doctor.

Other Information:store at room temperature 15° - 30°C (59° - 86°F)

INACTIVE INGREDIENT

Inactive Ingredients: Aloe barbadensis leaf extract, cetyl alcohol, glyceryl stearate SE, mineral oil, PEG-100 stearate, peppermint oil, phenoxyethanol, propylene glycol, purified water, stearyl alcohol, white petrolatum, xanthan gum

Questions? Comments?

1-855-361-3993

Manufactured for:

AvKARE, Pulaski, TN 38478

www.avkare.com

AV 06/22